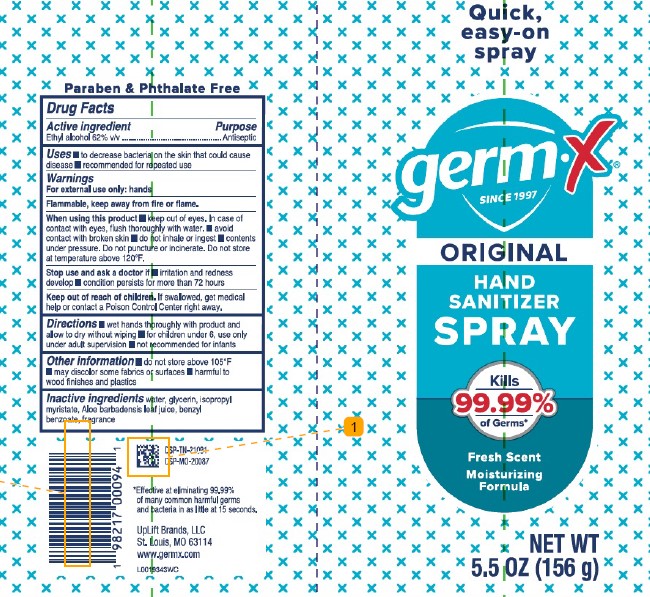 DRUG LABEL: Hand Sanitizer
NDC: 83986-199 | Form: SPRAY
Manufacturer: UpLift Brands, LLC
Category: otc | Type: HUMAN OTC DRUG LABEL
Date: 20250401

ACTIVE INGREDIENTS: ALCOHOL 62 mL/100 mL
INACTIVE INGREDIENTS: WATER; GLYCERIN; ISOPROPYL MYRISTATE; ALOE VERA LEAF; BENZYL BENZOATE

Germ-X 199.001/199AB
Hand Sanitizer Spray

Claims

Paraben & Phthalate Free

Active ingredient

Ethyl alcohol 62% v/v

Purpose

Antiseptic

Uses

- to decrease bacteria on the skin that could cause disease
- recommended for repeated use

Warnings

For external use only: hands

Flammable, keep away from fire or flame.

When using this product

- keep out of eyes. In case of contact with eyes, flush thoroughly with water.
- avoid contact with broken skin
- do not inhale or ingest
- contents under pressure. Do not puncture or incinerate. Do not store at temperature above 120°F.

Stop use and ask a doctor if

- irritation and redness develop
- condition persists for more than 72 hours

Keep out of reach children.

If swallowed, get medical help or contact a Poison Control Center right away.

Directions

- wet hands thoroughly with product and allow to dry without wiping
- for children under 6, use only under adult supervision
- not recommended for infants

Other information

- do not store above 105°F
- may discolor some fabrics or surfaces
- harmful to wood finishes and plastics

Inactive ingredients

water, glycerin, isopropyl myristate, Aloe barbadensis leaf juice, benzyl benzoate, fragrance

Disclaimer

DSP-TN-21091

DSP-MO-20087

*Effective at eliminating 99.99% of many common harmful germs and bacteria in as little as 15 seconds.

Adverse reaction

UpLift Brands, LLC

St. Louis, MO 63114

www.germx.com

Principal display panel

Quick, easy-on spray

germ-x®

SINCE 1997

ORIGINAL

HAND SANITIZER SPRAY

Kills 99.99% of Germs*

Fresh Scent

Moisturizing Formula

NET WT 5.5 OZ (156 g)